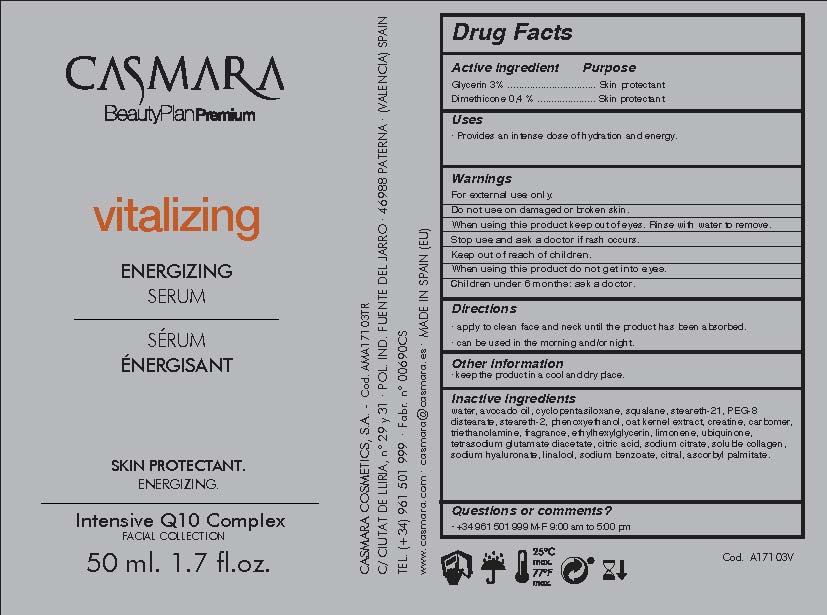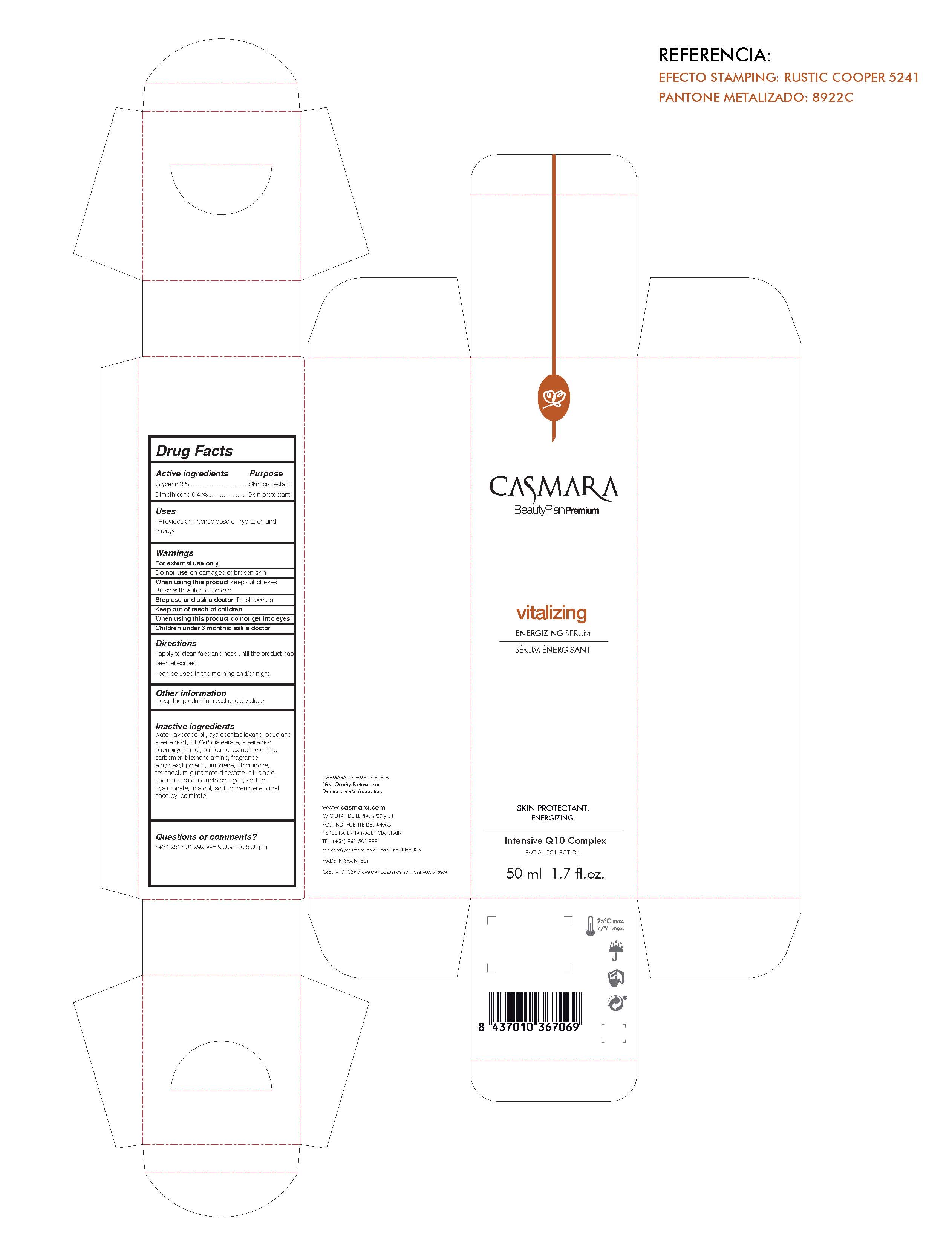 DRUG LABEL: Vitalizing Energizing Serum
NDC: 20151-087 | Form: CREAM
Manufacturer: Casmara Cosmetics, SA
Category: otc | Type: HUMAN OTC DRUG LABEL
Date: 20170223

ACTIVE INGREDIENTS: DIMETHICONE 0.4 mg/1 mL; GLYCERIN 3 mg/1 mL
INACTIVE INGREDIENTS: SODIUM BENZOATE 0.0125 mg/1 mL; SQUALANE 2 mg/1 mL; AVOCADO OIL 3 mg/1 mL; STEARETH-21 2 mg/1 mL; PEG-8 DISTEARATE 1.5 mg/1 mL; ASCORBYL PALMITATE 0.0012 mg/1 mL; SODIUM CITRATE 0.0275 mg/1 mL; HYALURONATE SODIUM 0.02 mg/1 mL; CYCLOMETHICONE 5 3 mg/1 mL; ETHYLHEXYLGLYCERIN 0.111 mg/1 mL; WATER 80.06851 mg/1 mL; PHENOXYETHANOL 0.94 mg/1 mL; TETRASODIUM GLUTAMATE DIACETATE 0.094 mg/1 mL; UBIQUINOL 0.1 mg/1 mL; PERFLUNAFENE 0.3 mg/1 mL; STEARETH-2 1.5 mg/1 mL; TROLAMINE 0.3 mg/1 mL; CREATINE 0.5 mg/1 mL; CITRIC ACID MONOHYDRATE 0.045 mg/1 mL; CARBOXYPOLYMETHYLENE 0.4 mg/1 mL; CITRAL 0.00147 mg/1 mL; LINALOOL, (+)- 0.0198 mg/1 mL; OAT KERNEL OIL 0.525 mg/1 mL; COLLAGEN, SOLUBLE, FISH SKIN 0.025 mg/1 mL; LIMONENE, (+)- 0.10497 mg/1 mL

Vitalizing Energizing Serum

WARNINGS

For external use only.

Do not use on damaged or broken skin.

When using this product keep our of the eyes. Rinse with water to remove.

Stop use and ask a doctor if rash occurs.

Keep out of reach of children.

Whhen using this product do not get into eyes.

Children under 6 months: as a doctor.

Stop use and ask a doctor if rash occurs

Children under 6 months: ask a doctor

. keep out of reach of children

Questions or comments? + 34 961 501 099 M-F 9:00 am to 5:00 pm

OTHER SAFETY INFORMATION

. keep the product in a cool and dry place

Directions

. apply every day gently onto clean face and neck until the product has been absorbed

. can be used in the morning and/or night

DOSAGE AND ADMINISTRATION

. apply every day gently onto clean dace and neck until the product has been absorbed

. can be used in the morning and/or night

Uses

. provides an intense dose of hydration and energy

INACTIVE INGREDIENT

water, avocado oil, cyclopentasiloxane, glycerin, squalane, steareth-21, PEG-8 distearate, steareth-2, phenoxyethanol, avena sativa (oat) kernel extract, craeline, carbomer, triethanolamine, perfume, ethylhexylglycerin, limonene, ubiquinone, tetrasodium glutamate diacetate, citric acid, sodium citrate, soluble collagen, sodium hyaluronte, linalool, sodium benzoate, citral, ascorbyl palmitate

PURPOSE

- provides an intense dose of hydration and energy

Active Ingredients

Glycerin 3.00%........................... Skin Protectant

Dimethicone 0.4%.......................Skin Protectant

PACKAGE LABEL

Vitalizing

Energizing Serum

Skin Protectant

Intensive Q10 Complex

Facial Collection